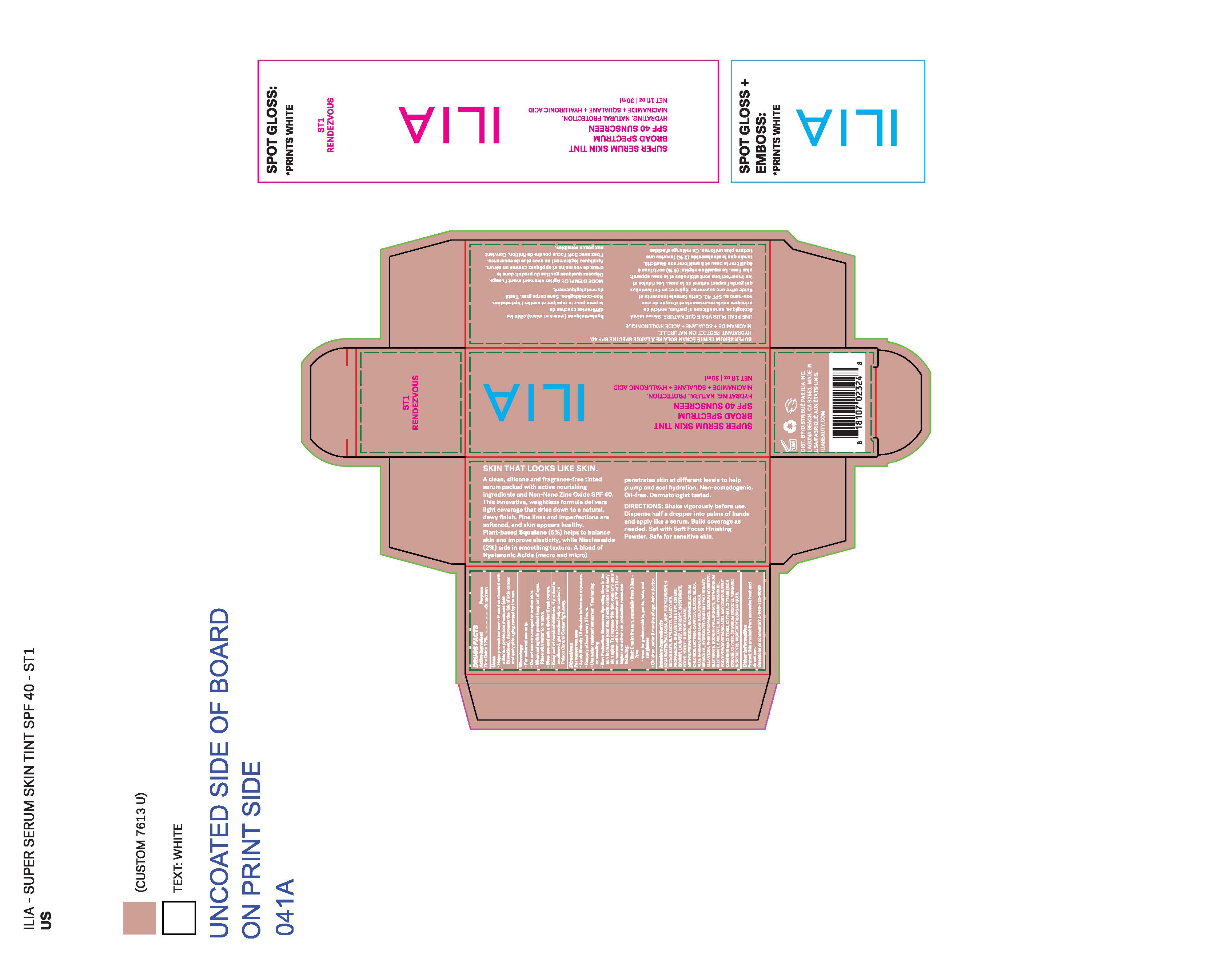 DRUG LABEL: ILIA SUPER SERUM SKIN TINT (ST1 RENDEZVOUS)
NDC: 81110-750 | Form: LOTION
Manufacturer: Ilia, Inc.
Category: otc | Type: HUMAN OTC DRUG LABEL
Date: 20251030

ACTIVE INGREDIENTS: ZINC OXIDE 132 mg/1 mL
INACTIVE INGREDIENTS: SHEA BUTTER; ISOAMYL LAURATE; POLYGLYCERYL-3 DIISOSTEARATE; ISOPROPYL ISOSTEARATE; .ALPHA.-BISABOLOL, (+)-; CAPRYLYL GLYCOL; LECITHIN, SOYBEAN; ALOE VERA LEAF; ALLANTOIN; SILICON DIOXIDE; SQUALANE; BUTYLOCTYL SALICYLATE; HYALURONATE SODIUM; TITANIUM DIOXIDE; SODIUM MYRISTOYL GLUTAMATE; ALUMINUM HYDROXIDE; WATER; NIACINAMIDE; PROPANEDIOL; SODIUM CHLORIDE; PHENYLPROPANOL; METHYLPROPANEDIOL

ILIA SUPER SERUM SKIN TINT (ST1 RENDEZVOUS)